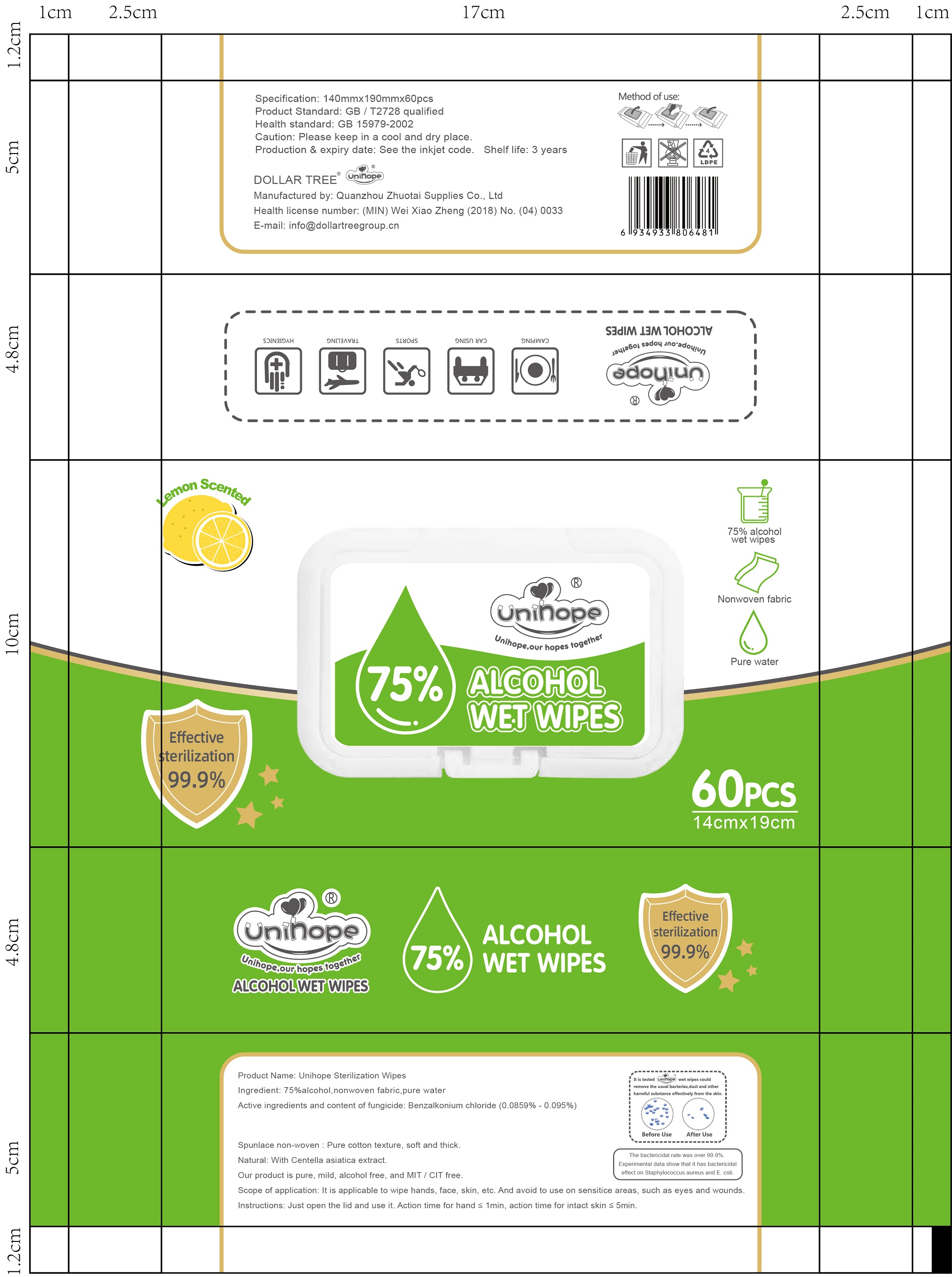 DRUG LABEL: Unihope Sterilization Wipes
NDC: 41636-100 | Form: CLOTH
Manufacturer: Quanzhou Zhuotai Supplies Co., Ltd.
Category: otc | Type: HUMAN OTC DRUG LABEL
Date: 20200731

ACTIVE INGREDIENTS: BENZALKONIUM CHLORIDE 85.9 mg/100 1; ALCOHOL 75 mL/100 1
INACTIVE INGREDIENTS: WATER

41636-100 Quanzhou zhuotai

Active Ingredient(s)

Alcohol 75%,Benzalkonium chloride(0.0859%-0.095%). Purpose: Antiseptic

Purpose

Spunlace non-woven:Pure cotton texture, soft and thick.Natural:with centella asiatica extract.Our product is pure ,mild,alcohol free,and mit/cit free.Scope of application;it is applicable to wipe hand ,face ,skin ,etc. and avoid to use on sensitice areas,such as eyes and wounds.
Instructions:Just open the lid and use it. Action time for hand ≤ 1min, action time for intact skin ≤ 5min.

Use

Spunlace non-woven:Pure cotton texture, soft and thick.Natural:with centella asiatica extract.Our product is pure ,mild,alcohol free,and mit/cit free.Scope of application;it is applicable to wipe hand ,face ,skin ,etc. and avoid to use on sensitice areas,such as eyes and wounds.
Instructions:Just open the lid and use it. Action time for hand ≤ 1min, action time for intact skin ≤ 5min.

Warnings

For external use only. Flammable. Keep away from heat or flame

Do not use

- in children less than 2 months of age
- on open skin wounds

When using this product keep out of eyes, ears, and mouth. In case of contact with eyes, rinse eyes thoroughly with water.
Stop use and ask a doctor if irritation or rash occurs. These may be signs of a serious condition.
Keep out of reach of children. If swallowed, get medical help or contact a Poison Control Center right away.

Stop use and ask a doctor if irritation or rash occurs. These may be signs of a serious condition.

Keep out of reach of children. If swallowed, get medical help or contact a Poison Control Center right away.

Directions

- Spunlace non-woven:Pure cotton texture, soft and thick.Natural:with centella asiatica extract.Our product is pure ,mild,alcohol free,and mit/cit free.Scope of application;it is applicable to wipe hand ,face ,skin ,etc. and avoid to use on sensitice areas,such as eyes and wounds.
  Instructions:Just open the lid and use it. Action time for hand ≤ 1min, action time for intact skin ≤ 5min.

Other information

- Store between 15-30C (59-86F)
- Avoid freezing and excessive heat above 40C (104F)

Inactive ingredients

Water